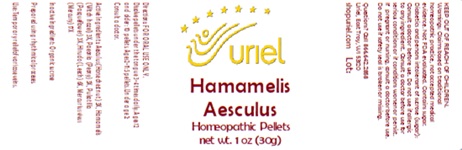 DRUG LABEL: Hamamelis Aesculus
NDC: 48951-5112 | Form: PELLET
Manufacturer: Uriel Pharmacy Inc
Category: homeopathic | Type: HUMAN OTC DRUG LABEL
Date: 20251010

ACTIVE INGREDIENTS: AESCULUS GLABRA NUT 3 [hp_X]/1 1; HAMAMELIS VIRGINIANA ROOT BARK/STEM BARK 3 [hp_X]/1 1; PAEONIA OFFICINALIS ROOT 3 [hp_X]/1 1; PULSATILLA VULGARIS 3 [hp_X]/1 1; DESIRUDIN 6 [hp_X]/1 1; MERCURY 17 [hp_X]/1 1
INACTIVE INGREDIENTS: SUCROSE

Hamamelis Aesculus Pellets

INDICATIONS AND USAGE

Directions: FOR ORAL USE ONLY.

DOSAGE AND ADMINISTRATION

Dissolve pellets under the tongue 3-4 times daily. Ages 12 and older: 10 pellets. Ages 2-11: 5 pellets. Under age 2: Consult a doctor.

ACTIVE INGREDIENT

Active Ingredients: Aesculus (Horse chestnut) 3X, Hamamelis (Witch hazel) 3X, Paeonia (Peony) 3X, Pulsatilla (Pasqueflower) 3X, Hirudo (Leech) 6X, Mercurius vivus (Mercury) 17X

Inactive Ingredient: Organic sucrose

Prepared using rhythmical processes.

PURPOSE

Use: Temporary relief of varicose veins.

KEEP OUT OF REACH OF CHILDREN.

WARNINGS

Warnings: Claims based on traditional homeopathic practice, not accepted medical evidence. Not FDA evaluated. Contains sugar. Diabetics and persons intolerant of sucrose (sugar): Consult a doctor before use. Do not use if allergic to any ingredient. Consult a doctor before use for serious conditions or if conditions worsen or persist. If you are pregnant or nursing, consult a doctor before use. Do not use if safety seal is broken or missing.

Questions? Call 866.642.2858
Uriel, East Troy, WI 53120
shopuriel.com Lot: